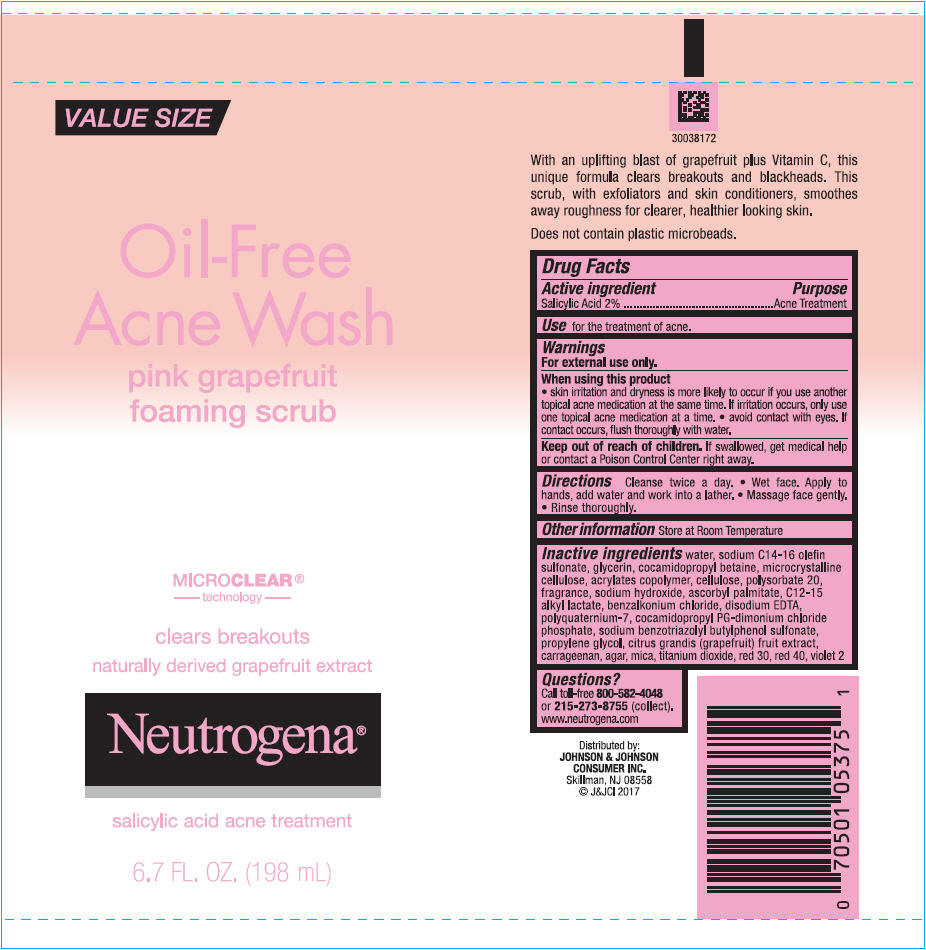 DRUG LABEL: Neutrogena Oil-Free Acne Wash Pink Grapefruit Foaming Scrub
NDC: 69968-0247 | Form: GEL
Manufacturer: Kenvue Brands LLC
Category: otc | Type: HUMAN OTC DRUG LABEL
Date: 20241111

ACTIVE INGREDIENTS: SALICYLIC ACID 20 mg/1 mL
INACTIVE INGREDIENTS: WATER; SODIUM C14-16 OLEFIN SULFONATE; GLYCERIN; COCAMIDOPROPYL BETAINE; MICROCRYSTALLINE CELLULOSE; BUTYL ACRYLATE/METHYL METHACRYLATE/METHACRYLIC ACID COPOLYMER (18000 MW); POLYSORBATE 20; POWDERED CELLULOSE; SODIUM HYDROXIDE; BENZALKONIUM CHLORIDE; C12-15 ALKYL LACTATE; EDETATE DISODIUM; POLYQUATERNIUM-7 (70/30 ACRYLAMIDE/DADMAC; 1600000 MW); COCAMIDOPROPYL PROPYLENE GLYCOL-DIMONIUM CHLORIDE PHOSPHATE; SODIUM BENZOTRIAZOLYL BUTYLPHENOL SULFONATE; CARRAGEENAN; AGAR, UNSPECIFIED; ASCORBYL PALMITATE; PROPYLENE GLYCOL; PUMMELO; MICA; D&C RED NO. 30; TITANIUM DIOXIDE; FD&C RED NO. 40; D&C VIOLET NO. 2

Neutrogena® Oil-Free Acne Wash pink grapefruit foaming scrub

Drug Facts

Active ingredients

Salicylic Acid 2%

Purpose

Acne treatment

Use

for the treatment of acne.

Warnings

For external use only.

When using this product

- skin irritation and dryness is more likely to occur if you use another topical acne medication at the same time. If irritation occurs, only use one topical acne medication at a time.
- avoid contact with eyes. If contact occurs, flush thoroughly with water.

Keep out of reach of children. If swallowed, get medical help or contact a Poison Control Center right away.

Directions

Cleanse twice a day.

- Wet face. Apply to hands, add water and work into a lather.
- Massage face gently.
- Rinse thoroughly.

Other information

Store at Room Temperature

Inactive ingredients

water, sodium C14-16 olefin sulfonate, glycerin, cocamidopropyl betaine, microcrystalline cellulose, acrylates copolymer, cellulose, Polysorbate 20, fragrance, sodium hydroxide, ascorbyl palmitate, C12-15 alkyl lactate, benzalkonium chloride, disodium EDTA, polyquaternuim-7, cocamidopropyl PG-dimonium chloride phosphate, sodium benzotriazolyl butylphenol sulfonate, propylene glycol, citrus grandis (grape fruit) fruit extract, carrageenan, agar, mica, titanium dioxide, red 30, red 40, violet 2.

Questions?

Call toll- free 800-582-4048 or 215-273-8755 (collect). www.neutrogena.com

Distributed by:
JOHNSON & JOHNSON
CONSUMER INC.
Skillman, NJ 08558

PRINCIPAL DISPLAY PANEL - 198 mL Tube Label

VALUE SIZE

Oil-Free
Acne Wash

pink grapefruit
foaming scrub

MICRO CLEAR ®
technology

clears breakouts
naturally derived grapefruit extract

Neutrogena®

salicylic acid acne treatment
6.7 FL.OZ. (198 mL)